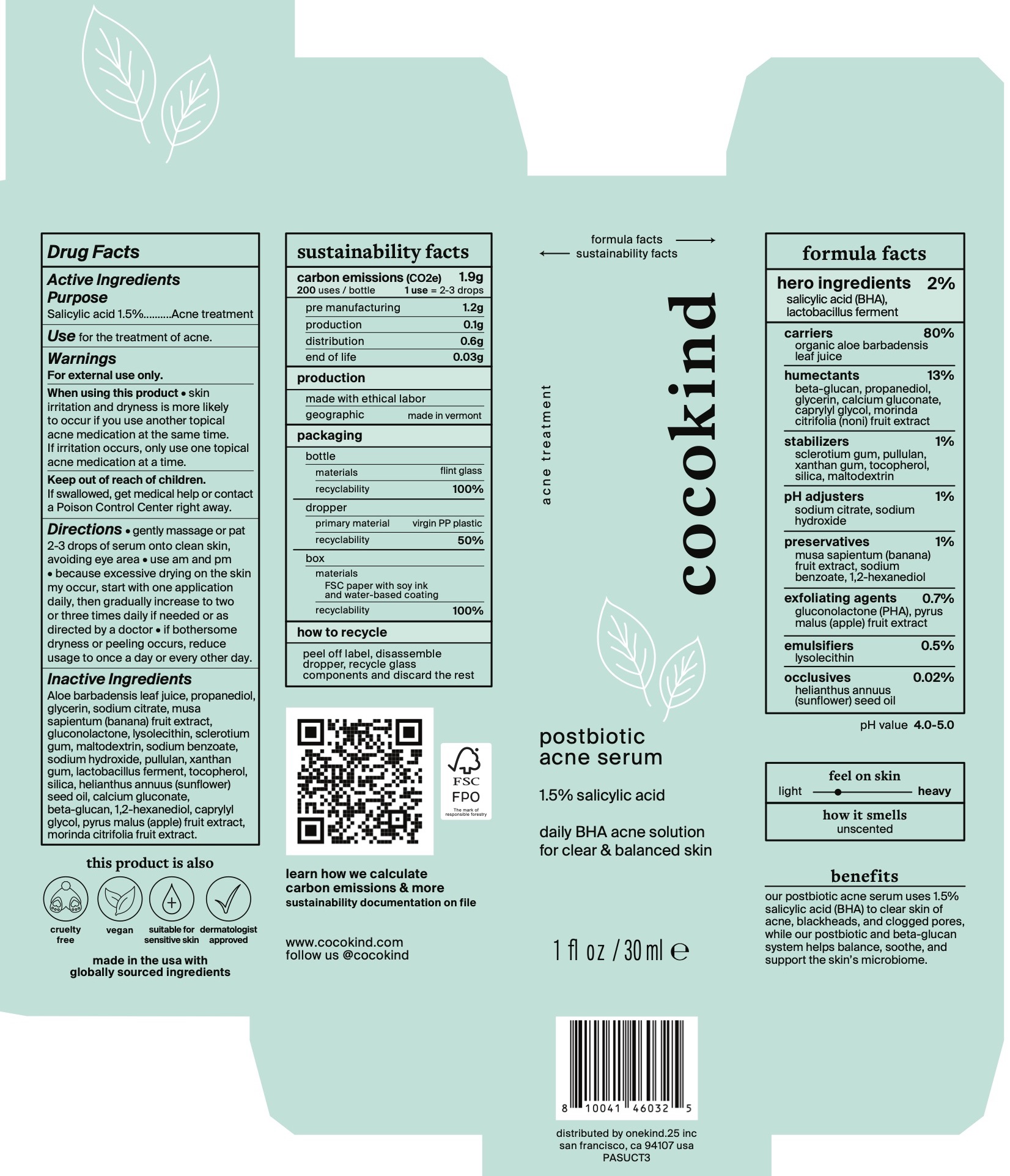 DRUG LABEL: Cocokind postbiotic acne serum
NDC: 79356-210 | Form: LIQUID
Manufacturer: Onekind.25
Category: otc | Type: HUMAN OTC DRUG LABEL
Date: 20251222

ACTIVE INGREDIENTS: SALICYLIC ACID 1.5 g/100 mL
INACTIVE INGREDIENTS: PULLULAN; SILICON DIOXIDE; SUNFLOWER OIL; CALCIUM GLUCONATE; APPLE; MORINDA CITRIFOLIA FRUIT; BETASIZOFIRAN; SODIUM HYDROXIDE; 1,2-HEXANEDIOL; CAPRYLYL GLYCOL; SODIUM BENZOATE; SODIUM CARBOXYMETHYL .BETA.-GLUCAN (DS 0.65-0.85); MALTODEXTRIN; ALOE VERA LEAF; PROPANEDIOL; BANANA; LACTOBACILLUS FERMENTUM; GLUCONOLACTONE; XANTHAN GUM; LYSOPHOSPHATIDYLCHOLINE, SOYBEAN; TOCOPHEROL; GLYCERIN; SODIUM CITRATE

Cocokind postbiotic acne serum

Active ingredient

Salicylic acid 1.5%.

Purpose

Acne treatment

Use

For the treatment of acne.

Warnings

For external use only.

When using this product skin irritation and dryness is more likely to occur if you use another topical acne medication at the same time. If irritation occurs, only use one topical acne medication at a time.

Keep out of reach of children. If swallowed, get medical help or contact a Poison Control Center right away.

DOSAGE AND ADMINISTRATION

• Gently massage or pat 2-3 drops of serum onto clean skin, avoiding eye area
• Use am and pm.
• Because excessive drying of the skin may occur, start with one application daily, then gradually increase to two to three times daily if needed or as directed by a doctor.
• If bothersome dryness or peeling occurs, reduce application to once a day or every other day.

Inactive ingredients

Aloe barbadensis leaf juice, propanediol, glycerin, sodium citrate, musa sapientum (banana) fruit extract, gluconolactone, lysolecithin, sclerotium gum, maltodextrin, sodium benzoate, sodium hydroxide, pullulan, xanthan gum, lactobacillus ferment, tocopherol, silica, helianthus annuus (sunflower) seed oil, calcium gluconate, beta-glucan, 1,2-hexanediol, caprylyl glycol, pyrus malus (apple) fruit extract, morinda citrifolia fruit extract.